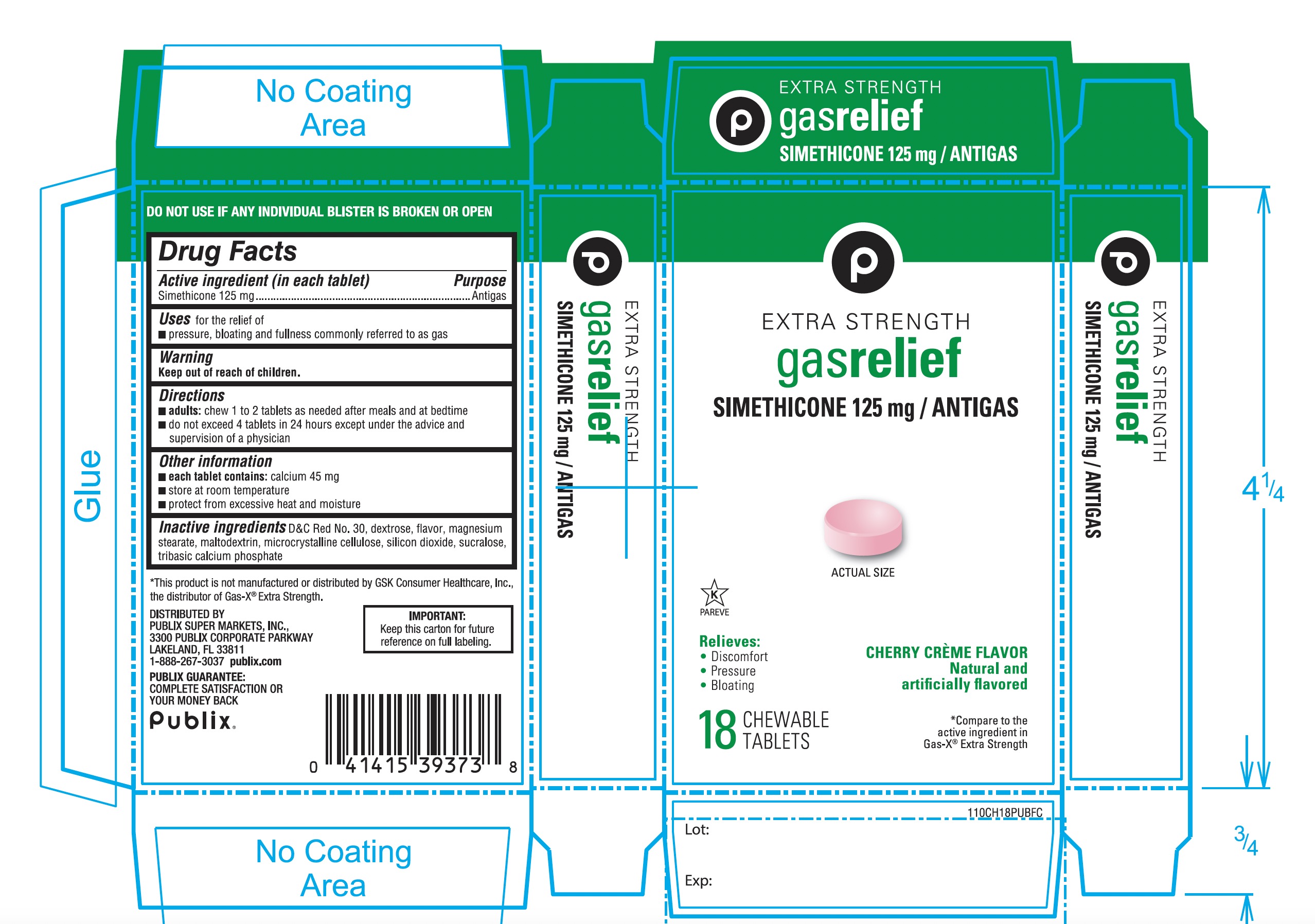 DRUG LABEL: Extra Strength gas relief
NDC: 41415-110 | Form: TABLET, CHEWABLE
Manufacturer: PUBLIX SUPER MARKETS, INC,
Category: otc | Type: HUMAN OTC DRUG LABEL
Date: 20251028

ACTIVE INGREDIENTS: DIMETHICONE, UNSPECIFIED 125 mg/1 1
INACTIVE INGREDIENTS: D&C RED NO. 30; DEXTROSE, UNSPECIFIED FORM; MAGNESIUM STEARATE; MALTODEXTRIN; MICROCRYSTALLINE CELLULOSE; SILICON DIOXIDE; SUCRALOSE; TRIBASIC CALCIUM PHOSPHATE

Publix Extra Strength gas relief Simethicone 125mg Cherry Crème Flavor 18 Chewable Tablets

Active ingredient (in each tablet)

Simethicone 125 mg

Purpose

Anti-gas

Uses for relief of

- pressure, bloating and fullness commonly referred to as gas.

Directions

- adults:chew 1 or 2 tablets as needed after meals and at bedtime
- do not exceed 4 tablets in 24 hours except under the advice and supervision of a physician.

Other information

- each tablet contains: calcium 45
- store at room temperature
- protect from excessive heat and moisture

Inactive ingredients

D&C Red No. 30, dextrose, flavor, magnesium stearate, maltodextrin, microcrystalline cellulose, silicon dioxide, sucralose, tribasic calcium phosphate

Questions or comments?

1-866-467-2748

Principal Display Panel

Publix

EXTRA STRENGTH

gas relief

SIMETHICONE 125 mg/ANTIGAS

CHERRY CREME FLAVOR

Natural and Artificially Flavored

- Relieves:

- Discomfort
- Pressure
- Bloating
- *Compare to the active ingredient in Gas-X®Extra Strength

18 CHEWABLE TABLETS

DO NOT USE IF ANY INDIVIDUAL BLISTER IS BROKEN OR OPEN

*This product is not manufactured or distributed by GSK Consumer Healthcare Inc., the distributor of GAS-X®Extra Strength.

DISTRIBUTED BY

3300 PUBLIX CORPORATE PARKWAY

PUBLIX SUPER MARKETS, INC,

LAKELAND,FL33811

Publix.com

PUBLIX GUARANTEE:

COMPLETE SATISFACTION OR YOUR MONEY BACK